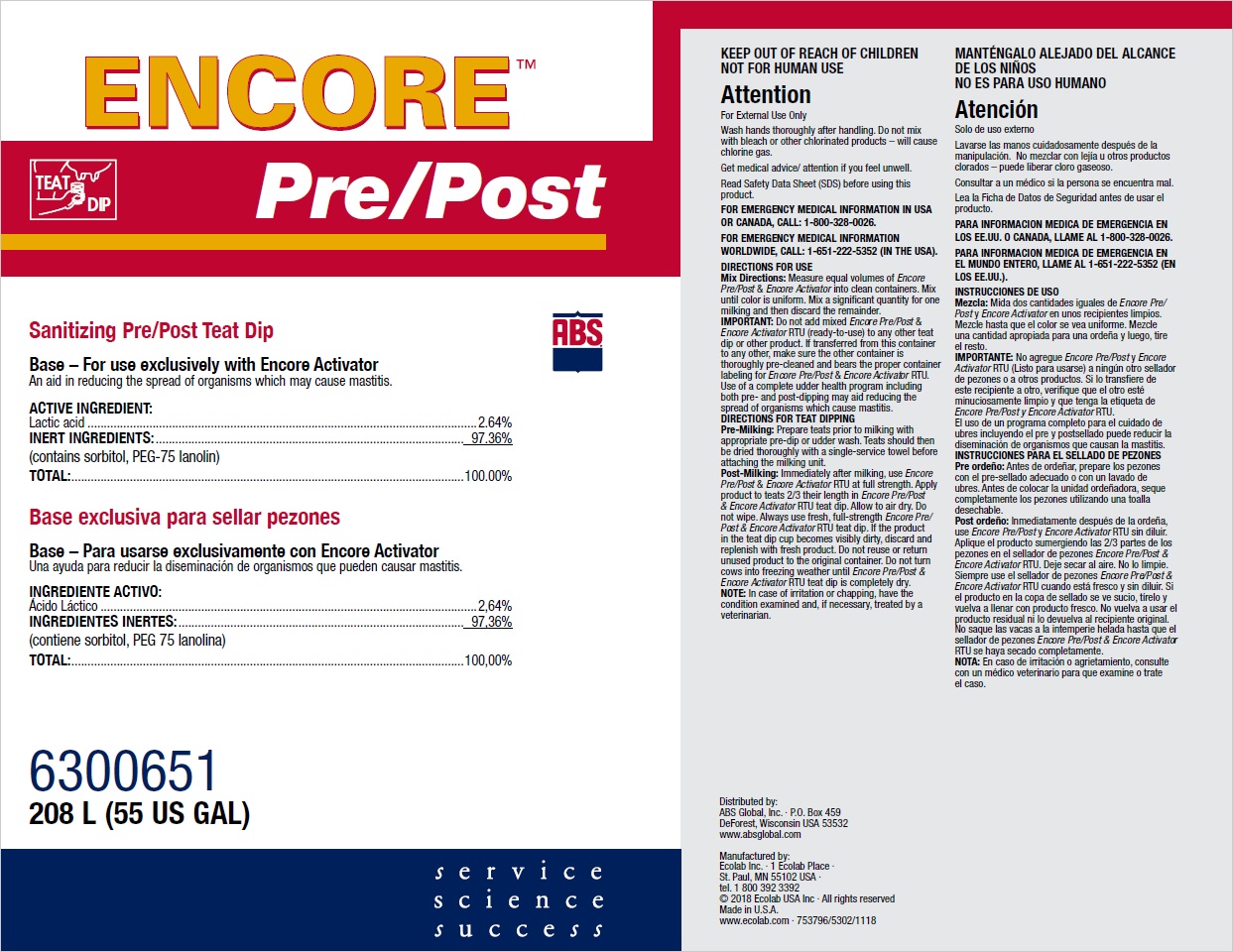 DRUG LABEL: Encore Pre/Post
NDC: 59282-107 | Form: SOLUTION
Manufacturer: ABS Global Inc.
Category: animal | Type: OTC ANIMAL DRUG LABEL
Date: 20190624

ACTIVE INGREDIENTS: LACTIC ACID 26.4 mg/1 mL
INACTIVE INGREDIENTS: WATER; SORBITOL; PEG-75 LANOLIN

KEEP OUT OF REACH OF CHILDREN

NOT FOR HUMAN USE

Attention

For External Use Only

Wash hands thoroughly after handling. Do not mix

with bleach or other chlorinated products – will cause

chlorine gas.

Get medical advice/ attention if you feel unwell.

Read Safety Data Sheet (SDS) before using this

product.

VETERINARY INDICATIONS

DIRECTIONS FOR USE

Mix Directions: Measure equal volumes of Encore

Pre/Post & Encore Activator into clean containers. Mix

until color is uniform. Mix a significant quantity for one

milking and then discard the remainder.

IMPORTANT: Do not add mixed Encore Pre/Post &

Encore Activator RTU (ready-to-use) to any other teat

dip or other product. If transferred from this container

to any other, make sure the other container is

thoroughly pre-cleaned and bears the proper container

labeling for Encore Pre/Post & Encore Activator RTU.

Use of a complete udder health program including

both pre- and post-dipping may aid reducing the

spread of organisms which cause mastitis.

DIRECTIONS FOR TEAT DIPPING

Pre-Milking: Prepare teats prior to milking with

appropriate pre-dip or udder wash. Teats should then

be dried thoroughly with a single-service towel before

attaching the milking unit.

Post-Milking: Immediately after milking, use Encore

Pre/Post & Encore Activator RTU at full strength. Apply

product to teats 2/3 their length in Encore Pre/Post

& Encore Activator RTU teat dip. Allow to air dry. Do

not wipe. Always use fresh, full-strength Encore Pre/

Post & Encore Activator RTU teat dip. If the product

in the teat dip cup becomes visibly dirty, discard and

replenish with fresh product. Do not reuse or return

unused product to the original container. Do not turn

cows into freezing weather until Encore Pre/Post &

Encore Activator RTU teat dip is completely dry.

NOTE: In case of irritation or chapping, have the

condition examined and, if necessary, treated by a

veterinarian.

FOR EMERGENCY MEDICAL INFORMATION IN USA

OR CANADA, CALL: 1-800-328-0026.

FOR EMERGENCY MEDICAL INFORMATION

WORLDWIDE, CALL: 1-651-222-5352 (IN THE USA).

Representative label and principal display panel

Pre/Post

Sanitizing Pre/Post Teat Dip

Base – For use exclusively with Encore Activator

An aid in reducing the spread of organisms which may cause mastitis.

ACTIVE INGREDIENT:

Lactic acid.........................................................................................................................2.64%

INERT INGREDIENTS:................................................................................................ 97.36%

(contains sorbitol, PEG-75 lanolin)

TOTAL:..........................................................................................................................100.00%

6300651

208 L (55 US GAL)

Distributed by:

ABS Global, Inc. ∙ P.O. Box 459

DeForest, Wisconsin USA 53532

www.absglobal.com

Manufactured by:

Ecolab Inc. ∙ 1 Ecolab Place ∙

St. Paul, MN 55102 USA ∙

tel. 1 800 392 3392

© 2018 Ecolab USA Inc ∙ All rights reserved

Made in U.S.A.

www.ecolab.com ∙ 753796/5302/1118